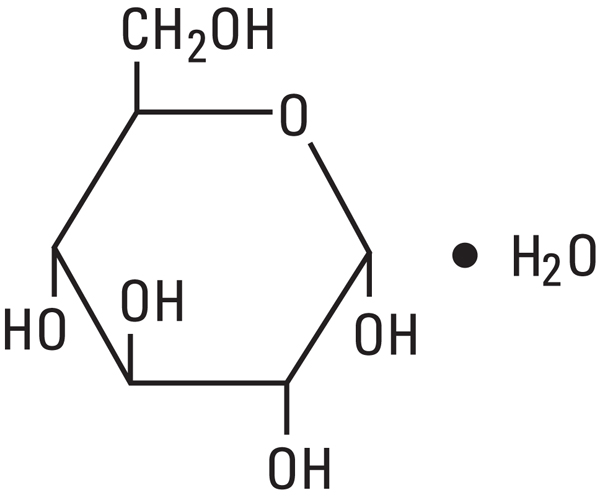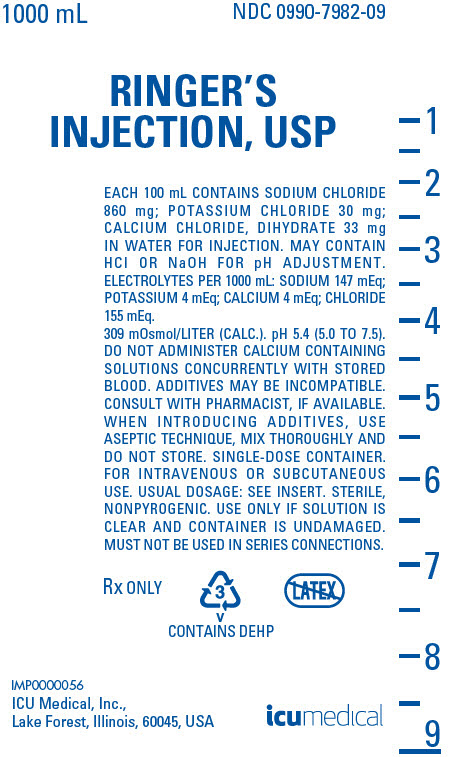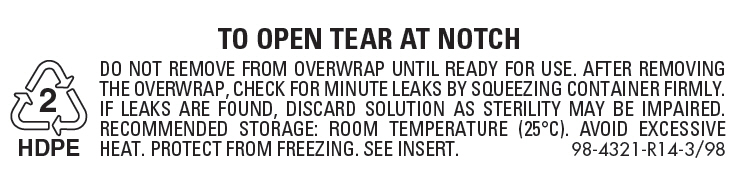 DRUG LABEL: Ringers
NDC: 0990-7982 | Form: INJECTION, SOLUTION
Manufacturer: ICU Medical, Inc.
Category: prescription | Type: HUMAN PRESCRIPTION DRUG LABEL
Date: 20251102

ACTIVE INGREDIENTS: POTASSIUM CHLORIDE 30 mg/100 mL; CALCIUM CHLORIDE 33 mg/100 mL; SODIUM CHLORIDE 860 mg/100 mL
INACTIVE INGREDIENTS: HYDROCHLORIC ACID; SODIUM HYDROXIDE; WATER

Ringer's Injection, USP

Flexible Plastic Container

Rx only

DESCRIPTION

This product is a sterile, nonpyrogenic solutions containing isotonic concentrations of electrolytes in water for injection. The solution is isotonic. The solution is administered by intravenous infusion for parenteral replacement of extracellular losses of fluid and electrolytes, with or without minimal carbohydrate calories.

Each 100 mL of Ringer's Injection, USP contains sodium chloride 860 mg, potassium chloride 30 mg and calcium chloride, dihydrate 33 mg. May contain hydrochloric acid and/or sodium hydroxide for pH adjustment. A liter provides 147 mEq sodium (Na^+), 4 mEq potassium (K^+), 4 mEq calcium (Ca^++) and 155 mEq chloride (Cl^−). The electrolyte content is isotonic (309 mOsmol/liter, calc.) in relation to the extracellular fluid (approx. 280 mOsmol/liter). The pH of the solution is 5.4 (5.0 − 7.5).

The solution contains no bacteriostat, antimicrobial agent or added buffer (except for pH adjustment) and is intended only for use as a single-dose injection. When smaller doses are required the unused portion should be discarded.

The solution is a parenteral fluid, nutrient and/or electrolyte replenisher.

Dextrose, USP is chemically designated D-glucose, monohydrate (C6H12O6 ∙ H2O), a hexose sugar freely soluble in water. It has the following structural formula:

Calcium Chloride, USP is chemically designated calcium chloride, dihydrate (CaCl2 ∙ 2 H2O), white fragments or granules freely soluble in water.

Potassium Chloride, USP is chemically designated KCl, a white granular powder freely soluble in water.

Sodium Chloride, USP is chemically designated NaCI, a white crystalline powder freely soluble in water.

Water for Injection, USP is chemically designated H2O.

The flexible plastic container is fabricated from a specially formulated polyvinylchloride. Water can permeate from inside the container into the overwrap but not in amounts sufficient to affect the solution significantly. Solution inside the plastic container also can leach out certain chemical components in very small amounts before the expiration period is attained. However, the safety of the plastic has been confirmed by tests in animals according to USP biological standards for plastic containers.

CLINICAL PHARMACOLOGY

When administered intravenously, this solution provides a source of water and electrolytes with or without minimal carbohydrate calories. The electrolyte content resembles that of the principal ionic constituents of normal plasma and the solution therefore is suitable for parenteral replacement of extracellular losses of fluid and electrolytes, with or without carbohydrate calories.

Calcium chloride in water dissociates to provide calcium (Ca^++) and chloride (Cl^−) ions. They are normal constituents of the body fluids and are dependent on various physiologic mechanisms for maintenance of balance between intake and output. Approximately 80% of body calcium is excreted in the feces as insoluble salts; urinary excretion accounts for the remaining 20%.

Potassium chloride in water dissociates to provide potassium (K^+) and chloride (Cl^−) ions. Potassium is found in low concentration in plasma and extracellular fluids (3.5 to 5.0 mEq/liter in a healthy adult). It is the chief cation of body cells (160 mEq/liter of intracellular water). Potassium plays an important role in electrolyte balance. Normally about 80 to 90% of the potassium intake is excreted in the urine; the remainder in the stools and to a small extent, in the perspiration. The kidney does not conserve potassium well so that during fasting or in patients on a potassium-free diet, potassium loss from the body continues resulting in potassium depletion.

Sodium chloride in water dissociates to provide sodium (Na^+) and chloride (Cl^−) ions. Sodium (Na^+) is the principal cation of the extracellular fluid and plays a large part in the therapy of fluid and electrolyte disturbances. Chloride (Cl^−) has an integral role in buffering action when oxygen and carbon dioxide exchange occurs in the red blood cells. The distribution and excretion of sodium (Na^+) and chloride (Cl^−) are largely under the control of the kidney which maintains a balance between intake and output.

Water is an essential constituent of all body tissues and accounts for approximately 70% of total body weight. Average normal adult daily requirement ranges from two to three liters (1.0 to 1.5 liters each for insensible water loss by perspiration and urine production).

Water balance is maintained by various regulatory mechanisms. Water distribution depends primarily on the concentration of electrolytes in the body compartments and sodium (Na^+) plays a major role in maintaining physiologic equilibrium.

INDICATIONS AND USAGE

This solution is indicated for parenteral replacement of extracellular losses of fluid and electrolytes, with or without minimal carbohydrate calories, as required by the clinical condition of the patient.

WARNINGS

Solutions containing calcium ions should not be administered simultaneously through the same administration set as blood because of the likelihood of coagulation.

Solutions which contain potassium should be used with great care, if at all, in patients with hyperkalemia, severe renal failure and in conditions in which potassium retention is present.

Solutions containing sodium ions should be used with great care, if at all, in patients with congestive heart failure, severe renal insufficiency and in clinical states in which there exists edema with sodium retention.

In patients with diminished renal function, administration of solutions containing sodium or potassium ions may result in sodium or potassium retention.

Solutions containing lactate ions should be used with great care in patients with metabolic or respiratory alkalosis. The administration of lactate ions should be done with great care where there is an increased level or an impaired utilization of lactate ions, as in severe hepatic insufficiency.

The intravenous administration of these solutions can cause fluid and/or solute overloading resulting in dilution of serum electrolyte concentrations, overhydration, congested states or pulmonary edema. The risk of dilutional states is inversely proportional to the electrolyte concentrations of administered parenteral solutions.

The risk of solute overload causing congested states with peripheral and pulmonary edema is directly proportional to the electrolyte concentrations of such solutions.

PRECAUTIONS

Clinical evaluation and periodic laboratory determinations are necessary to monitor changes in fluid balance, electrolyte concentrations and acid-base balance during prolonged parenteral therapy or whenever the condition of the patient warrants such evaluation.

Caution must be exercised in the administration of parenteral fluids, especially those containing sodium ions, to patients receiving corticosteroids or corticotropin.

Potassium containing solutions should be used with caution in the presence of cardiac disease, particularly in digitalized patients or in the presence of renal disease.

Solutions containing lactate ions should be used with caution as excess administration may result in metabolic alkalosis.

Do not administer unless solution is clear and container is undamaged. Discard unused portion.

Pregnancy Category C

Animal reproduction studies have not been conducted with Ringer's Injection, USP,. It is also not known whether this injection can cause fetal harm when administered to a pregnant woman or can affect reproduction capacity. This injection should be given to a pregnant woman only if clearly needed.

Pediatric Use

The safety and effectiveness in the pediatric population are based on the similarity of the clinical conditions of the pediatric and adult populations. In neonates or very small infants the volume of fluid may affect fluid and electrolyte balance.

ADVERSE REACTIONS

Reactions which may occur because of the solution or the technique of administration include febrile response, infection at the site of injection, venous thrombosis or phlebitis extending from the site of injection, extravasation and hypervolemia.

If an adverse reaction does occur, discontinue the infusion, evaluate the patient, institute appropriate therapeutic countermeasures and save the remainder of the fluid for examination if deemed necessary.

OVERDOSAGE

In the event of overhydration or solute overload, re-evaluate the patient and institute appropriate corrective measures. See WARNINGS, PRECAUTIONS, and ADVERSE REACTIONS.

DOSAGE AND ADMINISTRATION

The dose is dependent upon the age, weight and clinical condition of the patient.

Drug Interactions

Additives may be incompatible. Consult with pharmacist, if available. When introducing additives, use aseptic technique, mix thoroughly and do not store.

The presence of calcium limits their compatibility with certain drugs that form precipitates of calcium salts, and also prohibits their simultaneous infusion through the same administration set as blood because of the likelihood of coagulation.

Parenteral drug products should be inspected visually for particulate matter and discoloration prior to administration, whenever solution and container permit. See PRECAUTIONS.

INSTRUCTIONS FOR USE

To Open:

Tear outer wrap at notch and remove solution container. If supplemental medication is desired, follow directions below before preparing for administration. Some opacity of the plastic due to moisture absorption during the sterilization process may be observed. This is normal and does not affect the solution quality or safety. The opacity will diminish gradually.

To Add Medication

1. Prepare additive port.
2. Using aseptic technique and an additive delivery needle of appropriate length, puncture resealable additive port at target area, inner diaphragm and inject. Withdraw needle after injecting medication.
3. The additive port may be protected by covering with an additive cap.
4. Mix container contents thoroughly.

Preparation for Administration

(Use aseptic technique)

1. Close flow control clamp of administration set.
2. Remove cover from outlet port at bottom of container.
3. Insert piercing pin of administration set into port with a twisting motion until the set is firmly seated. NOTE: See full directions on administration set carton.
4. Suspend container from hanger.
5. Squeeze and release drip chamber to establish proper fluid level in chamber.
6. Open flow control clamp and clear air from set. Close clamp.
7. Attach set to venipuncture device. If device is not indwelling, prime and make venipuncture.
8. Regulate rate of administration with flow control clamp.

WARNING: DO NOT USE FLEXIBLE CONTAINER IN SERIES CONNECTIONS.

HOW SUPPLIED

This solution is supplied in a single-dose flexible plastic container as follows:

NDC No. | Product Name | Container Size (mL)
0409–7982–09 | Ringer's Inj., USP | 1000
0990-7982-09 | Ringer's Inj., USP | 1000

ICU Medical is transitioning NDC codes from the "0409" to a "0990" labeler code. Both NDC codes are expected to be in the market for a period of time.

Protect from freezing. Store at 20 to 25°C (68 to 77°F). [See USP Controlled Room Temperature.]

Revised: March, 2020

IFU0000173

ICU Medical, Inc., Lake Forest, Illinois, 60045, USA

PRINCIPAL DISPLAY PANEL - 1000 mL Bag Label

1000 mL
NDC 0990-7982-09

RINGER'S
INJECTION, USP

EACH 100 mL CONTAINS SODIUM CHLORIDE
860 mg; POTASSIUM CHLORIDE 30 mg;
CALCIUM CHLORIDE, DIHYDRATE 33 mg
IN WATER FOR INJECTION. MAY CONTAIN
HCl OR NaOH FOR pH ADJUSTMENT.
ELECTROLYTES PER 1000 mL: SODIUM 147 mEq;
POTASSIUM 4 mEq; CALCIUM 4 mEq; CHLORIDE
155 mEq.

309 mOsmol/LITER (CALC.). pH 5.4 (5.0 TO 7.5).
DO NOT ADMINISTER CALCIUM CONTAINING
SOLUTIONS CONCURRENTLY WITH STORED
BLOOD. ADDITIVES MAY BE INCOMPATIBLE.
CONSULT WITH PHARMACIST, IF AVAILABLE.
WHEN INTRODUCING ADDITIVES, USE
ASEPTIC TECHNIQUE, MIX THOROUGHLY AND
DO NOT STORE. SINGLE-DOSE CONTAINER.
FOR INTRAVENOUS OR SUBCUTANEOUS
USE. USUAL DOSAGE: SEE INSERT. STERILE,
NONPYROGENIC. USE ONLY IF SOLUTION IS
CLEAR AND CONTAINER IS UNDAMAGED.
MUST NOT BE USED IN SERIES CONNECTIONS.

Rx ONLY

3
V
CONTAINS DEHP

IMP0000056
ICU Medical, Inc.,
Lake Forest, Illinois, 60045, USA

icumedical

PRINCIPAL DISPLAY PANEL - 1000 mL Bag Overwrap

TO OPEN TEAR AT NOTCH

2
HDPE

DO NOT REMOVE FROM OVERWRAP UNTIL READY FOR USE. AFTER REMOVING
THE OVERWRAP, CHECK FOR MINUTE LEAKS BY SQUEEZING CONTAINER FIRMLY.
IF LEAKS ARE FOUND, DISCARD SOLUTION AS STERILITY MAY BE IMPAIRED.
RECOMMENDED STORAGE: ROOM TEMPERATURE (25°C). AVOID EXCESSIVE
HEAT. PROTECT FROM FREEZING. SEE INSERT.
98-4321-R14-3/98